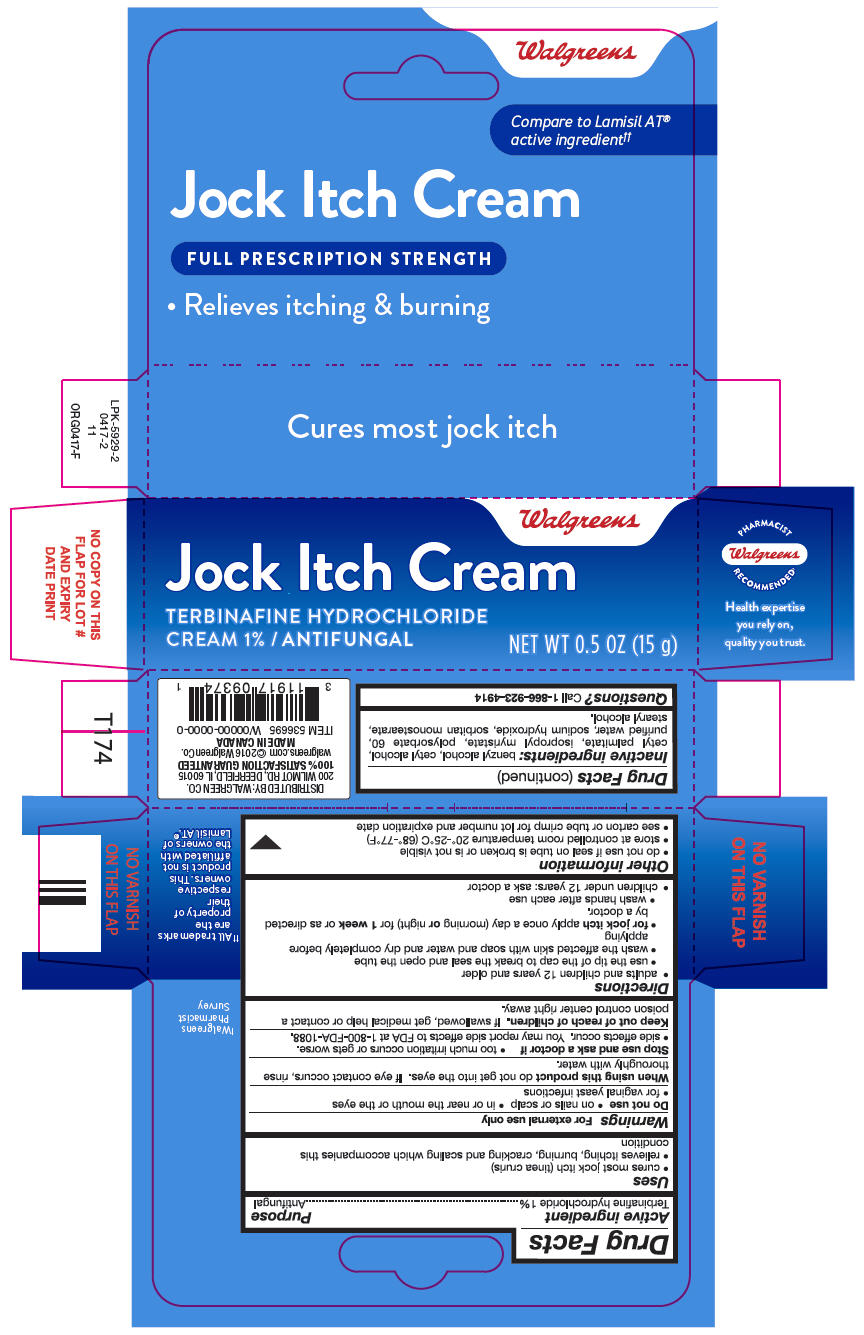 DRUG LABEL: Terbinafine Hydrochloride
NDC: 0363-2083 | Form: CREAM
Manufacturer: Walgreen Company
Category: otc | Type: HUMAN OTC DRUG LABEL
Date: 20170717

ACTIVE INGREDIENTS: Terbinafine Hydrochloride 1 g/100 g
INACTIVE INGREDIENTS: benzyl alcohol; cetyl alcohol; cetyl palmitate; isopropyl myristate; polysorbate 60; water; sodium hydroxide; sorbitan monostearate; stearyl alcohol

Terbinafine Hydrochloride

Drug Facts

Active ingredient

Terbinafine hydrochloride 1%

Purpose

Antifungal

Uses

- cures most jock itch (tinea cruris)
- relieves itching, burning, cracking and scaling which accompanies this condition

Warnings

For external use only

Do not use

- on nails or scalp
- in or near the mouth or the eyes
- for vaginal yeast infections

When using this product do not get into the eyes. If eye contact occurs, rinse thoroughly with water.

Stop use and ask a doctor if

- too much irritation occurs or gets worse.
- side effects occur. You may report side effects to FDA at 1-800-FDA-1088.

Keep out of reach of children. If swallowed, get medical help or contact a poison control center right away.

Directions

- adults and children 12 years and older
  - use the tip of the cap to break the seal and open the tube
  - wash the affected skin with soap and water and dry completely before applying
  - for jock itch apply once a day (morning or night) for 1 week or as directed by a doctor.
  - wash hands after each use
- children under 12 years: ask a doctor

Other information

- do not use if seal on tube is broken or is not visible
- store at controlled room temperature 20°-25°C (68°-77°F)
- see carton or tube crimp for lot number and expiration date

Inactive ingredients

benzyl alcohol, cetyl alcohol, cetyl palmitate, isopropyl myristate, polysorbate 60, purified water, sodium hydroxide, sorbitan monostearate, stearyl alcohol.

Questions?

Call 1-866-923-4914

DISTRIBUTED BY: WALGREEN CO.
200 WILMOT RD., DEERFIELD, IL 60015

PRINCIPAL DISPLAY PANEL - 15 g Tube Carton

Walgreens

Jock Itch Cream

TERBINAFINE HYDROCHLORIDE
CREAM 1% / ANTIFUNGAL

NET WT 0.5 OZ (15 g)